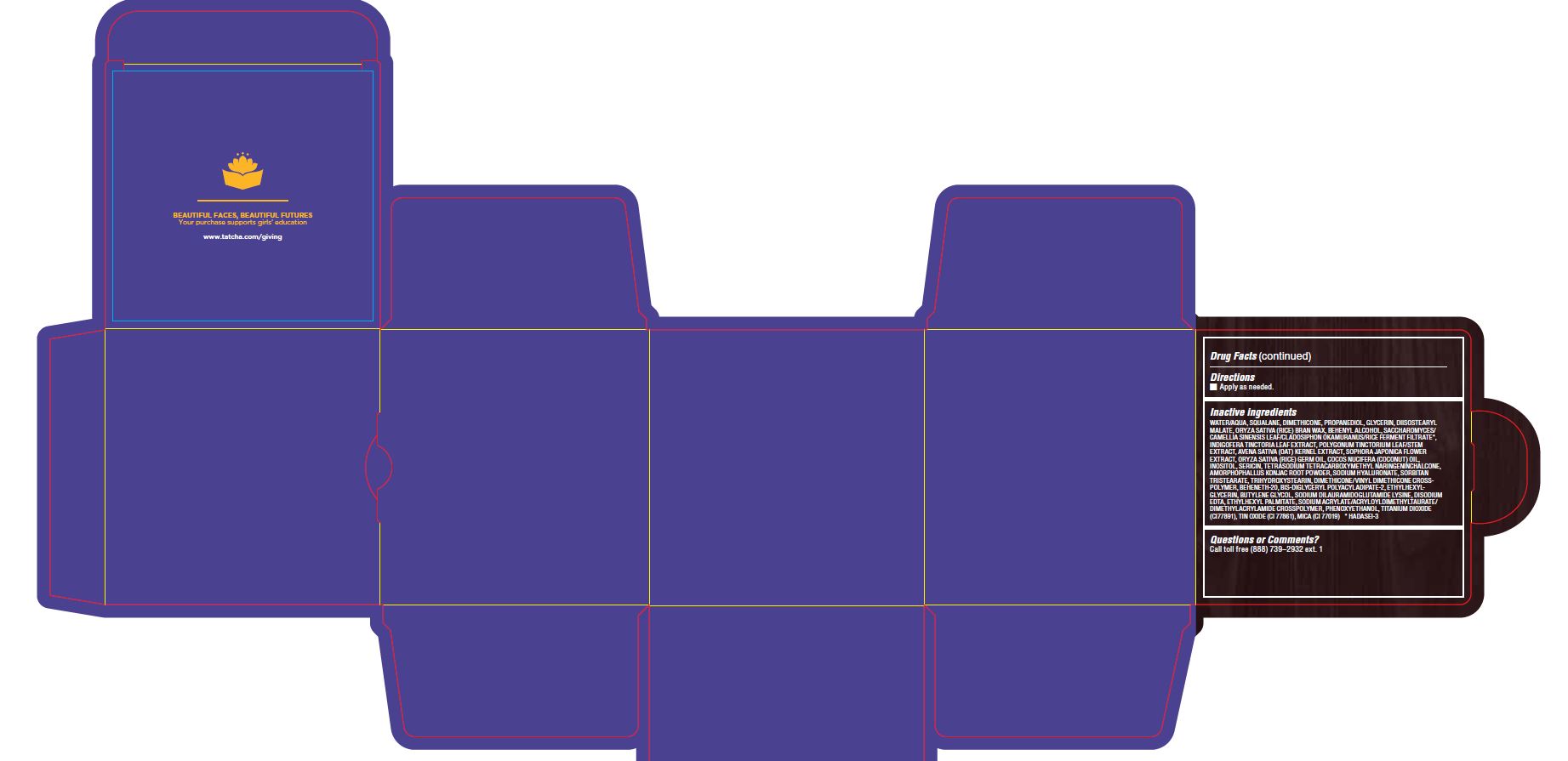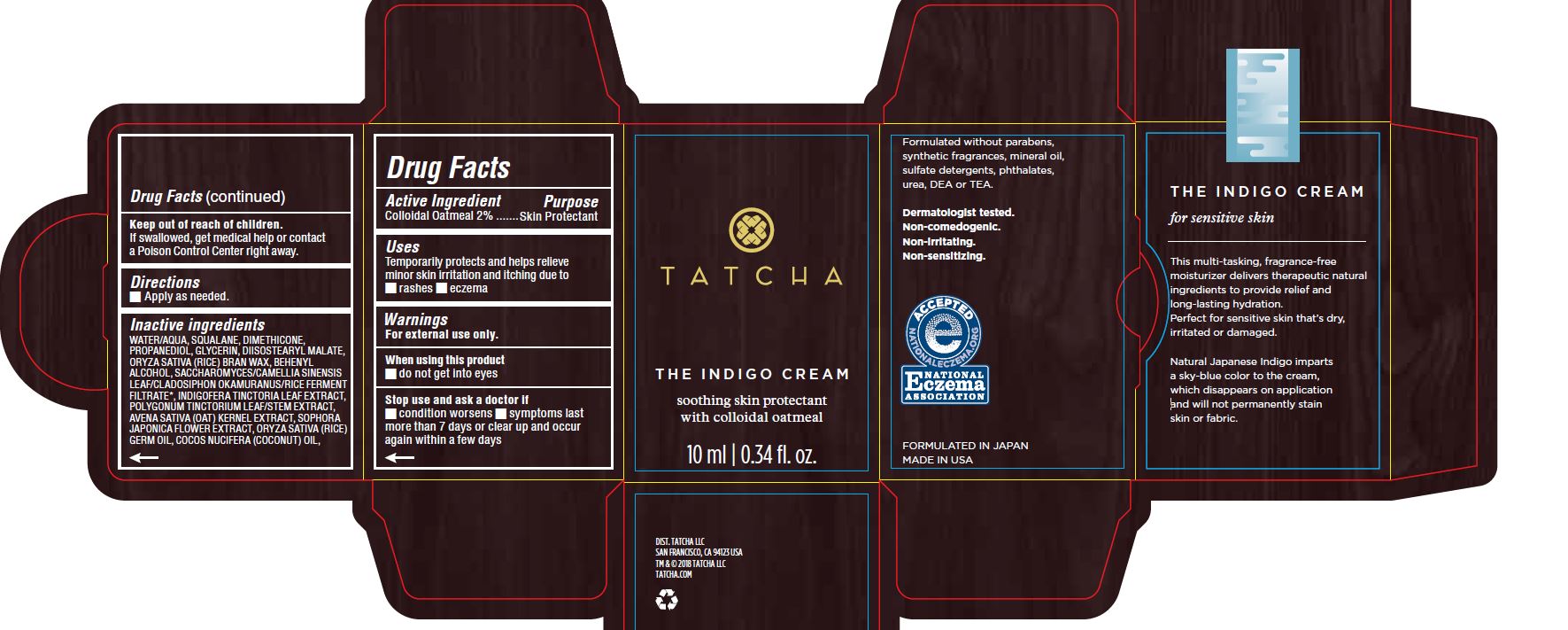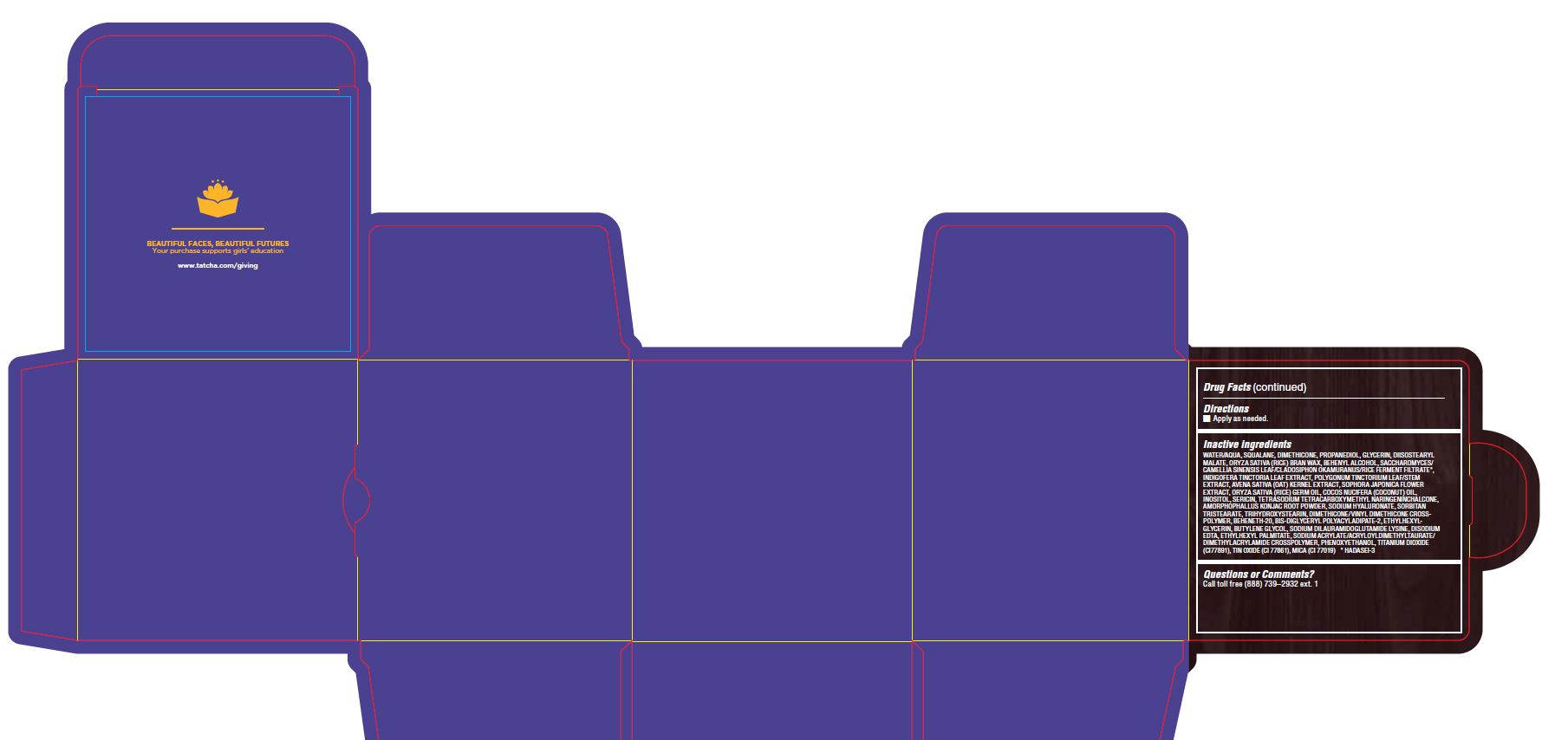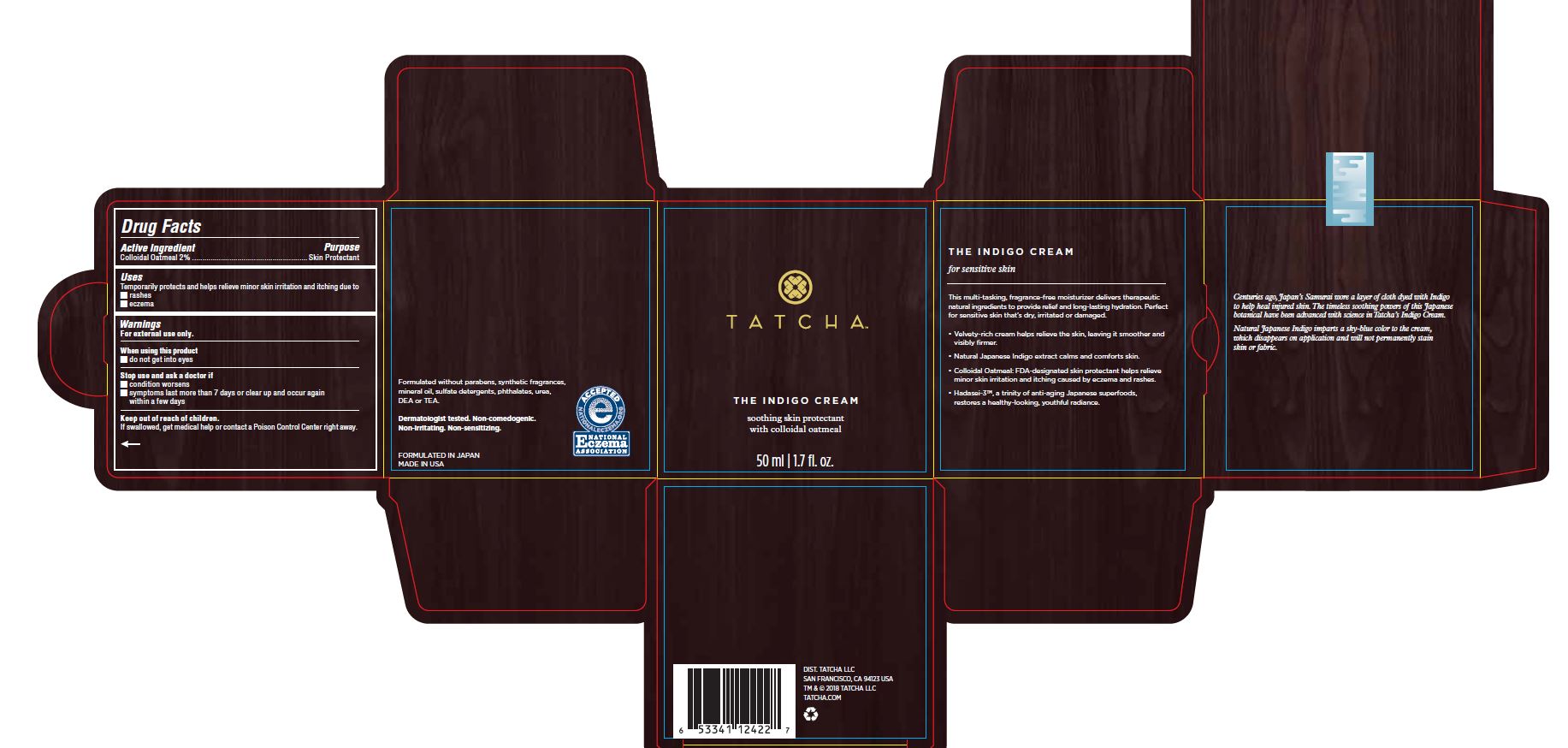 DRUG LABEL: The Indigo Cream
NDC: 69417-120 | Form: CREAM
Manufacturer: TATCHA, Inc.
Category: otc | Type: HUMAN OTC DRUG LABEL
Date: 20220131

ACTIVE INGREDIENTS: OATMEAL 2 mg/1 g
INACTIVE INGREDIENTS: WATER; SQUALANE; DIMETHICONE CROSSPOLYMER (450000 MPA.S AT 12% IN CYCLOPENTASILOXANE); PROPANEDIOL; GLYCERIN; DIISOSTEARYL MALATE; RICE BRAN; DOCOSANOL; CAMELLIA SINENSIS WHOLE; INDIGOFERA TINCTORIA LEAF; PERSICARIA TINCTORIA LEAF; OAT KERNEL OIL; STYPHNOLOBIUM JAPONICUM FLOWER; RICE GERM OIL; COCONUT OIL; INOSITOL; SERICIN 1; AMORPHOPHALLUS KONJAC ROOT; HYALURONATE SODIUM; SORBITAN TRISTEARATE; TRIHYDROXYSTEARIN; DIMETHICONE/VINYL DIMETHICONE CROSSPOLYMER (SOFT PARTICLE); BEHENETH-20; BIS-DIGLYCERYL POLYACYLADIPATE-2; ETHYLHEXYLGLYCERIN; BUTYLENE GLYCOL; DISODIUM EDTA-COPPER; ETHYLHEXYL PALMITATE; SODIUM ACRYLATE; PHENOXYETHANOL; TITANIUM DIOXIDE; STANNIC OXIDE; MICA

THE INDIGO CREAM

Drug Facts

Active Ingredients

Colloidal Oatmeal 2%

Purpose

Skin Protectant

Uses

Temporarily protects and helps relieve minor skin irritation and itching due to

- rashes
- eczema

Warnings

For external use only.

When using this product

- do not get into eyes

Stop use and ask a doctor if

- condition worsens
- symptoms last more than 7 days or clear up and occur again within a few days

Keep out of reach of children.

If swallowed, get medical help or contact a Poison Control Center right away.

Directions

- Apply as needed.

Inactive ingredients

WATER/AQUA, SQUALANE, DIMETHICONE, PROPANEDIOL, GLYCERIN, DIISOSTEARYL MALATE, ORYZA SATIVA (RICE) BRAN WAX, BEHENYL ALCOHOL, SACCHAROMYCES/CAMELLIA SINENSIS LEAF/CLADOSIPHON OKAMURANUS/RICE FERMENT FILTRATE*, INDIGOFERA TINCTORIA LEAF EXTRACT, POLYGONUM TINCTORIUM LEAF/STEM EXTRACT, AVENA SATIVA (OAT) KERNEL EXTRACT, SOPHORA JAPONICA FLOWER EXTRACT, ORYZA SATIVA (RICE) GERM OIL, COCOS NUCIFERA (COCONUT) OIL, INOSITOL, SERICIN, TETRASODIUM TETRACARBOXYMETHYL NARINGENINCHALCONE, AMORPHOPHALLUS KONJAC ROOT POWDER, SODIUM HYALURONATE, SORBITAN TRISTEARATE, TRIHYDROXYSTEARIN, DIMETHICONE/VINYL DIMETHICONE CROSSPOLYMER, BEHENETH-20, BIS-DIGLYCERYL POLYACYLADIPATE-2, ETHYLHEXYLGLYCERIN, BUTYLENE GLYCOL, SODIUM DILAURAMIDOGLUTAMIDE LYSINE, DISODIUM EDTA, ETHYLHEXYL PALMITATE, SODIUM ACRYLATE/ACRYLOYLDIMETHYLTAURATE/ DIMETHYLACRYLAMIDE CROSSPOLYMER, PHENOXYETHANOL, TITANIUM DIOXIDE (CI77891), TIN OXIDE (CI 77861), MICA (CI 77019) * HADASEI-3

Questions or Comments?

Call toll free (888) 739-2932 ext. 1

PACKAGE LABEL

TATCHA

THE INDIGO CREAM

soothing skin protectant with colloidal oatmeal

10 [50] ml/0.34 [1.7] fl. oz.